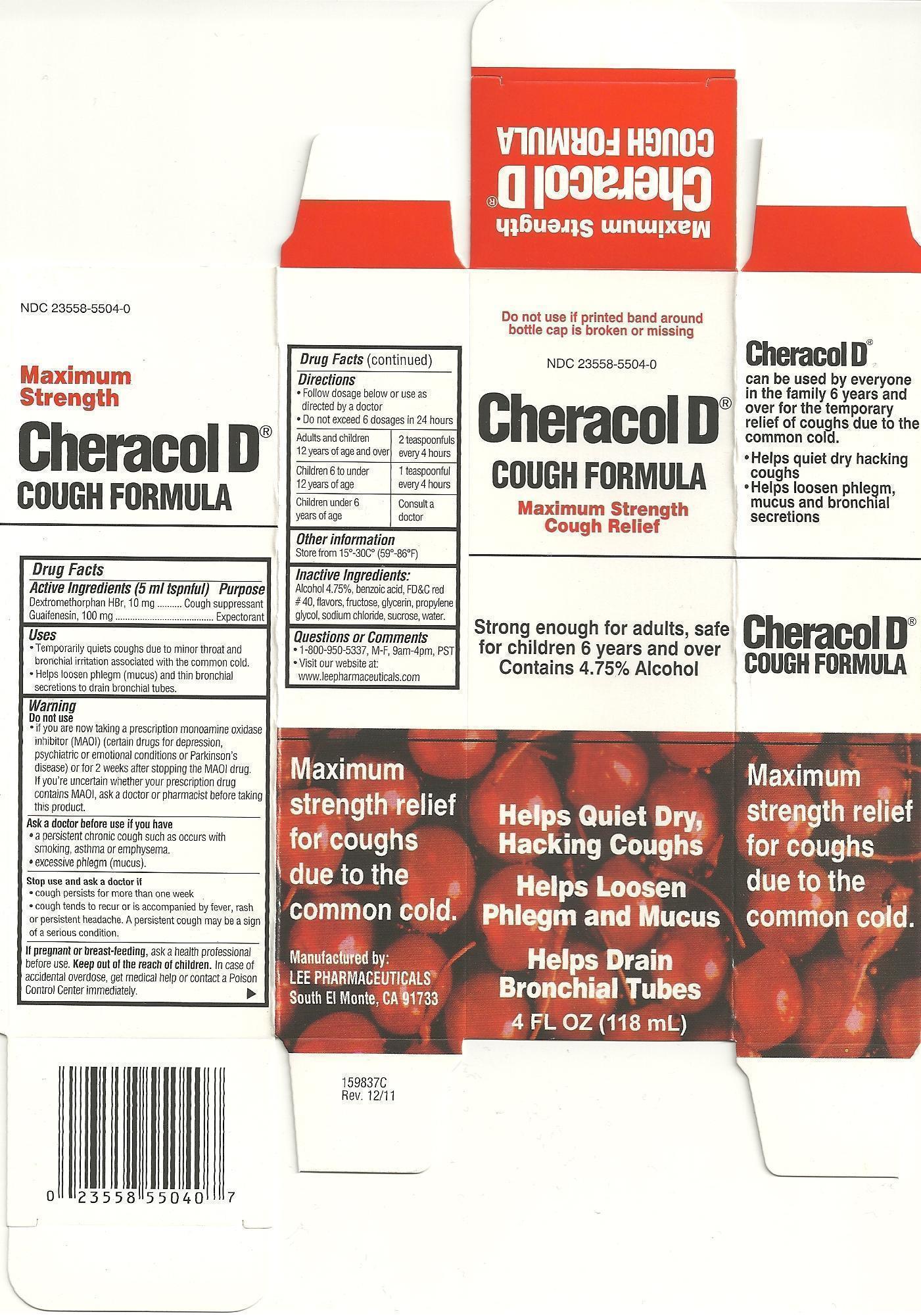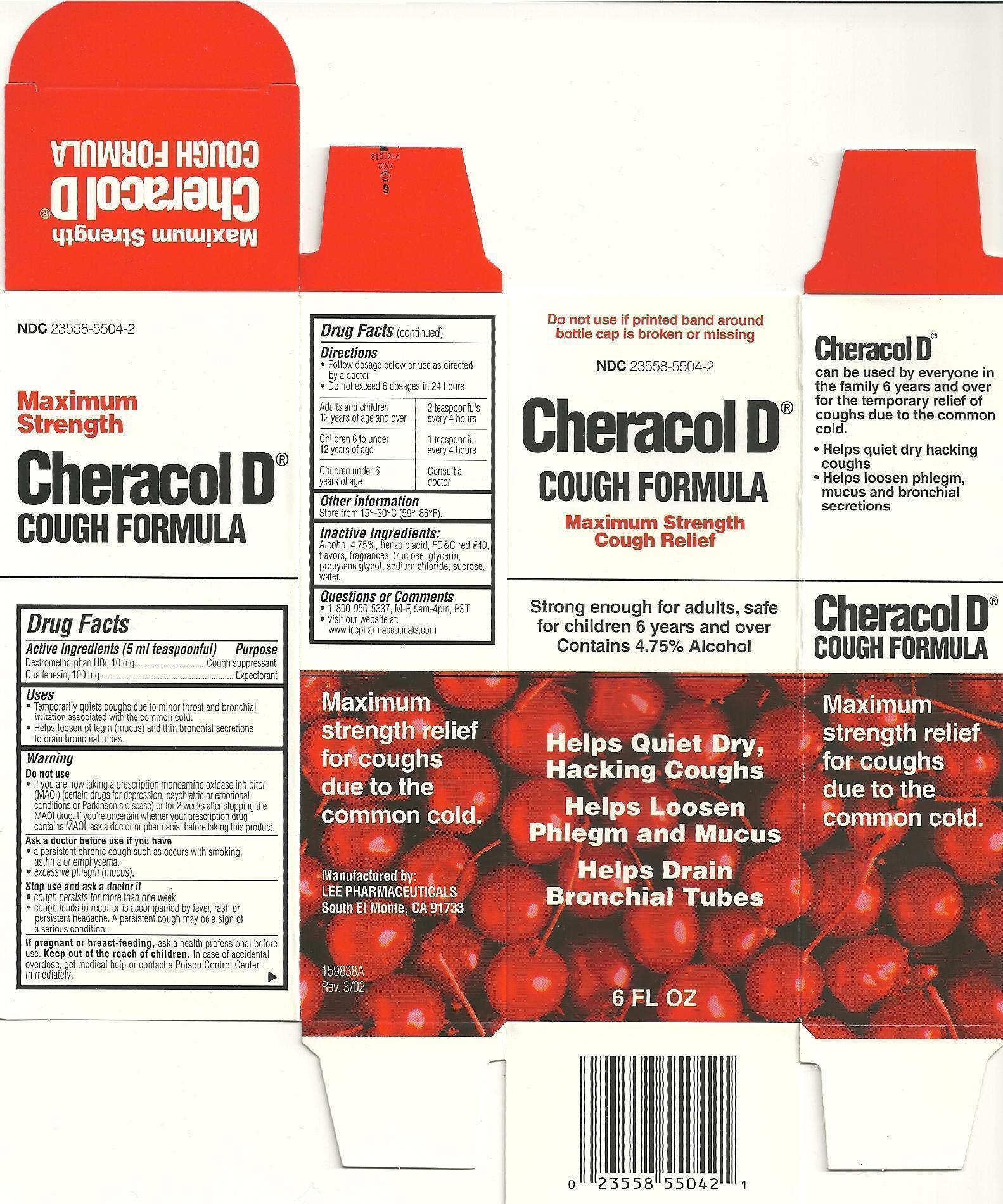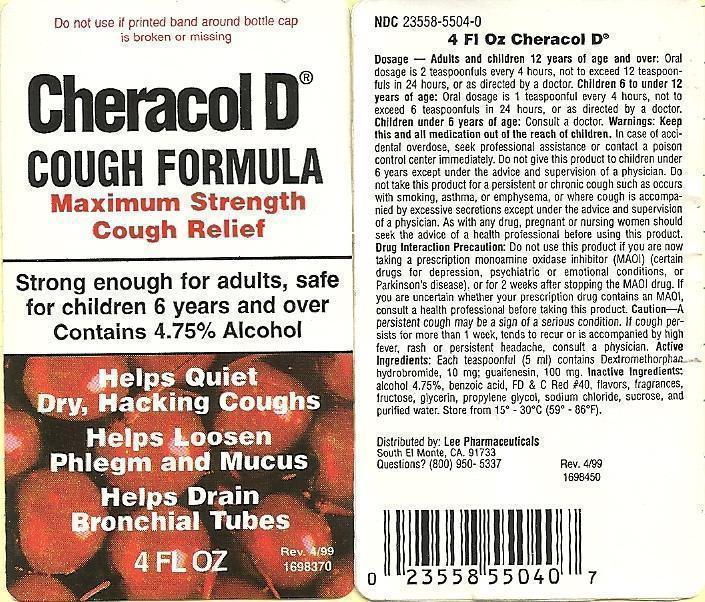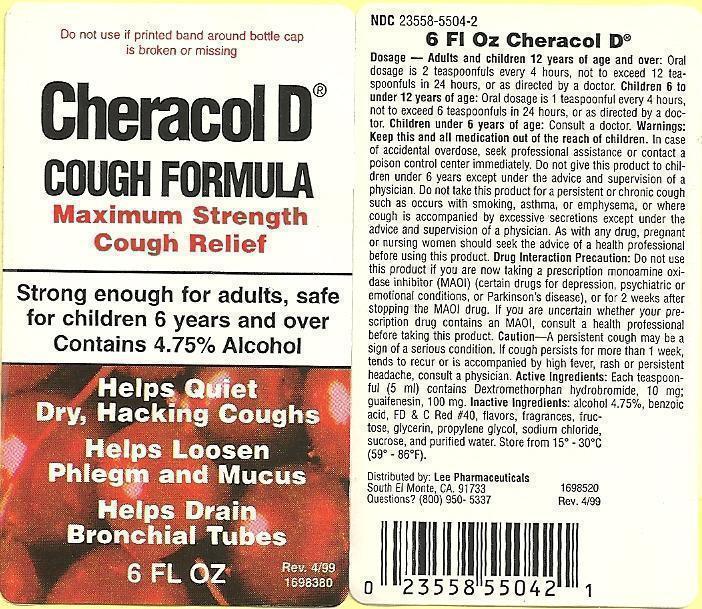 DRUG LABEL: Cheracol D
NDC: 23558-5504 | Form: SYRUP
Manufacturer: Lee Pharmaceuticals
Category: otc | Type: HUMAN OTC DRUG LABEL
Date: 20131206

ACTIVE INGREDIENTS: DEXTROMETHORPHAN HYDROBROMIDE 10 mg/5 mL; GUAIFENESIN 100 mg/5 mL
INACTIVE INGREDIENTS: FD&C RED NO. 40; GLYCERIN; PROPYLENE GLYCOL; WATER; FRUCTOSE; SODIUM CHLORIDE; SUCROSE; BENZOIC ACID; ALCOHOL

Drug Facts

Active ingredients (5 mL teaspoonful)

Dextromethorphan HBr, 10mg

Guaifenesin, 100mg

Purpose

Cough suppressant

Expectorant

Uses

- Temporarily quiets coughs due to minor throat and bronchial irritation associated with the common cold.
- Helps loosen phlegm (mucus) and thin bronchial secretions to drain bronchial tubes.

Warnings

Do not use

- if you are now taking a perscription monoamine oxidase inhibitor (MAOI) (certain drugs for depression, psychiatric or emotional conditions or Parkinson's disease) or for 2 weeks after stopping the MAOI drug. If you're uncertain whether your prescription drug contains MAOI, ask a doctor or pharmacist before taking this product.

Ask a doctor before use if you have

- a persistent chronic cough such as occurs with smoking, asthma or emphysema.
- excessive phlegm (mucus).

Stop use and ask a doctor if

- cough persists for more than one week
- cough tends to recur or is accompanied by fever, rash or persistent headache. A persistent cough may be a sign of a serious condition.

PREGNANCY OR BREAST FEEDING

If pregnant or breast-feeding, ask a health professional before use.

Keep out of reach of children. In case of accidental overdose, get medical help or contact a Poison Control Center immediately.

Directions

- Follow dosage below or use as directed by a doctor
- Do not exceed 6 dosages in 24 hours
- Adults and children 12 years or age and over, 2 teaspoonfuls every 4 hours
- Children 6 to under 12 years of age, 1 teaspoonful every 4 hours
- Children under 6 years of age, consult a doctor

Other information

Store from 15° - 30°C (59° - 86°F)

Inactive ingredients

Alcohol 4.75%, benzoic acid, FD&C red #40, flavors, fructose, glycerin, propylene glycol, sodium chloride, sucrose, water.

Questions or Comments

- 1-800-950-5337, M-F, 9am-4pm, PST
- Visit our website at: www.leepharmaceuticals.com